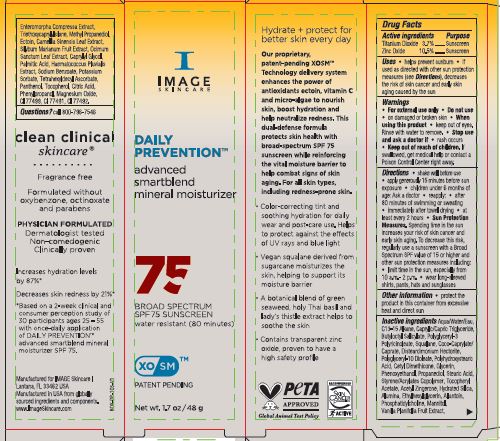 DRUG LABEL: Daily Prevention Advanced Smartblend Mineral Moisturizer SPF 75
NDC: 62742-4256 | Form: CREAM
Manufacturer: Allure Labs
Category: otc | Type: HUMAN OTC DRUG LABEL
Date: 20240320

ACTIVE INGREDIENTS: ZINC OXIDE 10.5 g/100 g; TITANIUM DIOXIDE 3.7 g/100 g
INACTIVE INGREDIENTS: ALUMINUM OXIDE; C13-15 ALKANE; COCO-CAPRYLATE/CAPRATE; DISTEARDIMONIUM HECTORITE; METHYLPROPANEDIOL; TOCOPHEROL; PHENYLPROPANOL; TETRAHEXYLDECYL ASCORBATE; PROPANEDIOL; ETHYLHEXYLGLYCERIN; POLYGLYCERYL-3 PENTARICINOLEATE; PHENOXYETHANOL; STEARIC ACID; ULVA COMPRESSA; HOLY BASIL LEAF; FERROSOFERRIC OXIDE; POLYGLYCERYL-10 DIOLEATE; POLYHYDROXYSTEARIC ACID (2300 MW); CETYL DIMETHICONE 45; GLYCERIN; STYRENE/ACRYLAMIDE COPOLYMER (MW 500000); .ALPHA.-TOCOPHEROL ACETATE; HYDRATED SILICA; ECTOINE; CAPRYLYL GLYCOL; ACETYL ZINGERONE; MANNITOL; FERRIC OXIDE YELLOW; TRIETHOXYCAPRYLYLSILANE; PALMITIC ACID; POTASSIUM SORBATE; CITRIC ACID MONOHYDRATE; FERRIC OXIDE RED; WATER; ALLANTOIN; PHOSPHATIDYLCHOLINE TRANSLOCATOR ABCB4; VANILLA BEAN; MAGNESIUM OXIDE; MEDIUM-CHAIN TRIGLYCERIDES; MILK THISTLE; HAEMATOCOCCUS PLUVIALIS; SODIUM BENZOATE; SQUALANE; GREEN TEA LEAF; PANTHENOL

Drug Facts

Active ingredients

Titanium Dioxide 3.7%

Zinc Oxide 10.5%

Purpose :Sunscreen

INDICATIONS AND USAGE

Uses ■ helps prevent sunburn • if used as directed with other sun protection measures (see Directions), decreases the risk of skin cancer and early skin aging caused by the sun.

Warnings • For external use only

Do not use • on damaged or broken skin

When using this product • keep out of eyes. Rinse with water to remove.

Stop use and ask a doctor if • rash occurs

Keep out of reach of children. If swallowed, get medical help or contact a Poison Control Center right away.

DOSAGE AND ADMINISTRATION

Directions • shake well before use • apply generousty15 minutes before sun exposure • children under 6 months of age:Ask a doctor • reapply: • after 80 minutes of swimming or sweating • immediately after towel drying • at least every 2 hours • Sun Protection Measures. Spending time in the sun increases your risk of skin cancer and early skin aging. To decrease this risk, regularly use a sunscreen with a Broad Spectrum SPF value of 15 or higher and other sun protection measures including: • limit time in the sun, especially from 10 a.m.- 2 p.m. • wear long-sleeved shirts, pants, hats and sunglasses

Other information • protect the product in this container from excessive heat and direct sun

INACTIVE INGREDIENT

Inactive ingredients: Aqua/water/Eau, C13-15 Alkane, Caprylic/Capric Triglyceride, Butyloctyl Salicylate, Polyglyceryl-3 Polyricinoleate, Squalane, Coco-Caprylate/ Caprate, Disteardimonium Hectorite, Polyglyceryl-10 Dioleate, Polyhydroxystearic Acid, Cetyl Dimethicone, Glycerin, Phenoxyethanol, Propanediol, Stearic Acid, Styrene/Acrylates Copolymer, Tocopheryl Acetate, Acetyl Zingerone, Hydrated Silica, Alumina, Ethylhexylglycerin, Allantoin, Phosphatidylcholine, Mannitol, Vanilla Planifolia Fruit Extract, Enteromorpha Compressa Extract, Triethoxycaprysilane, Methyl Propanediol, Ectoin, Camellia Sinensis Leaf Extract, Silybum Marianum Fruit Extract, Ocimum Sanctum Leaf Extract, Caprylyl Glycol, Palmitic Acid, Haematococcus Pluvialis Extract, Sodium Benzoate, Potassium Sorbate, Tetrahexyldecyl Ascorbate, Panthenol, Tocopherol, citric Acid, Phenylpropanol, Magnesium Oxide, CI 77499, CI 77491, CI 77492.